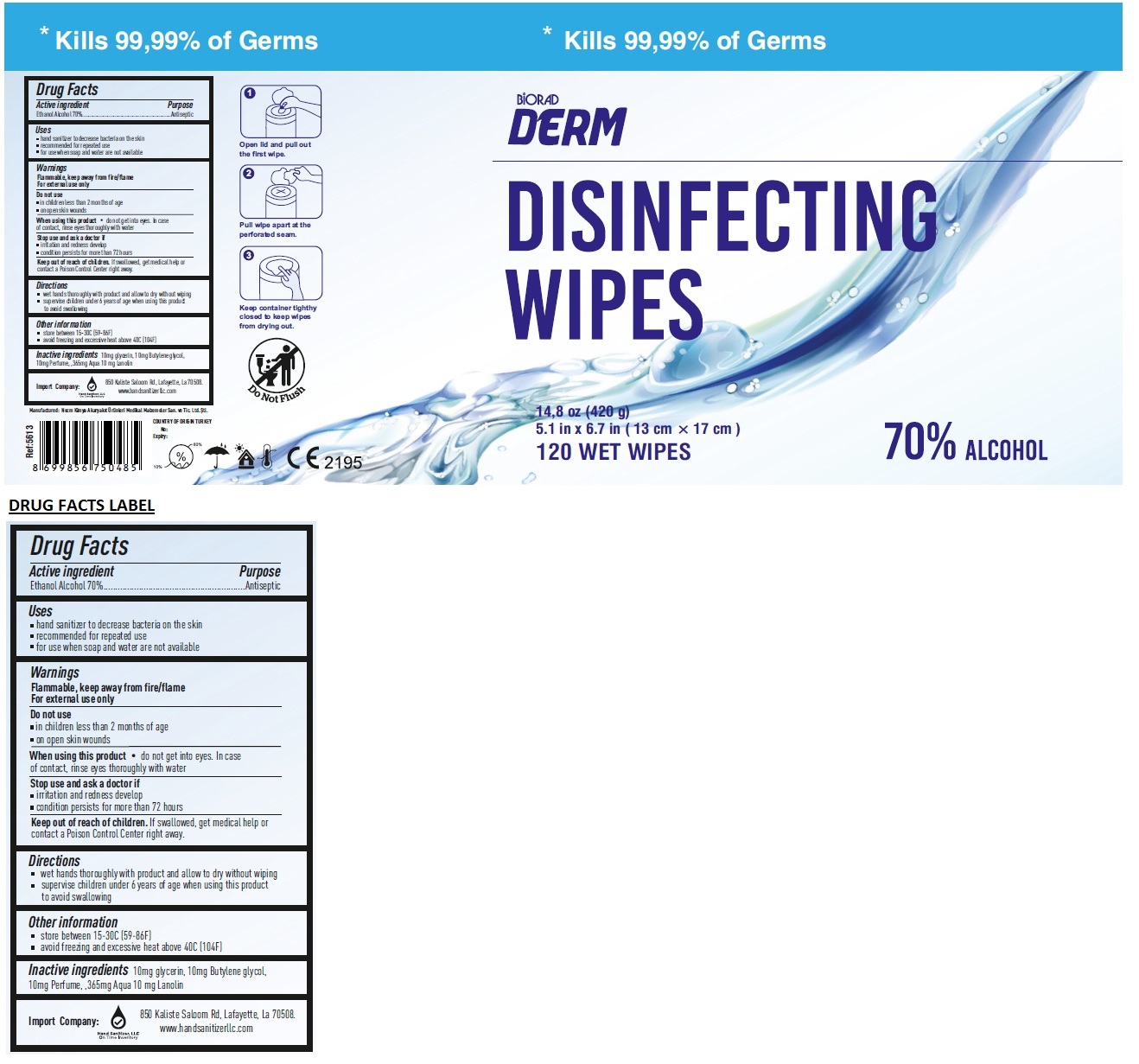 DRUG LABEL: DISINFECTING WIPES
NDC: 79455-002 | Form: CLOTH
Manufacturer: NECM KIMYA AKARYAKIT URUNLERI MEDIKAL MALZEMELER SANAYI VE TICARET LIMITED SIRKETI
Category: otc | Type: HUMAN OTC DRUG LABEL
Date: 20200713

ACTIVE INGREDIENTS: ALCOHOL 70 mL/100 mL
INACTIVE INGREDIENTS: GLYCERIN; BUTYLENE GLYCOL; WATER; LANOLIN

BiORAD DERM DISINFECTING WIPES

Active ingredient

Ethanol Alcohol 70%

Purpose

Antiseptic

Uses

- hand sanitizer to decrease bacteria on the skin
- recommended for repeated use
- for use when soap and water are not available

Warnings

Flammable, keep away from fire/flame

For external use only

Do not use

- in children less than 2 months of age
- on open skin wounds

When using this product • do not get into eyes. In case of contact, rinse eyes thoroughly with water

Stop use and ask a doctor if

- irritation and redness develop
- condition persists for more than 72 hours

Keep out of reach of children. If swallowed, get medical help or contact a Poison Control Center right away.

Directions

- wet hands thoroughly with product and allow to dry without wiping
- supervise children under 6 years of age when using this product to avoid swallowing

Other information

- store between 15-30C (59-86F)
- avoid freezing and excessive heat above 40C (104F)

Inactive ingredients

10mg glycerin, 10mg Butylene glycol, 10mg Perfume, ,365mg Aqua 10 mg Lanolin

Kills 99,99% of Germs

Import Company:

Hand Sanitizer, LLC

On Time Inventory

850 Kaliste Saloom Rd, Lafayette, La 70508.

www.handsanitizerllc.com

Manufactured: Necm Kimya Akaryakıt Ürünleri Medikal Malzemeler San. ve Tic. Ltd. Şti.

COUNTRY OF ORIGIN TURKEY

Open lid and pull out the first wipe.

Pull wipe apart at the perforated seam.

Keep container tighthy closed to keep wipes from drying out.

Do Not Flush